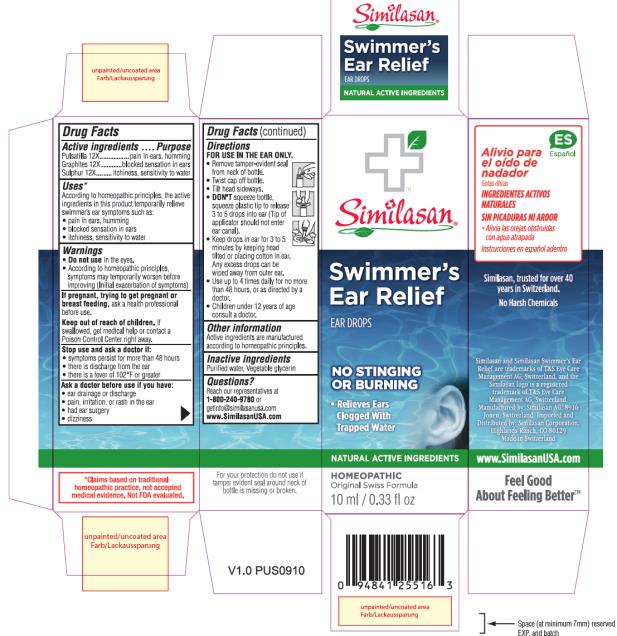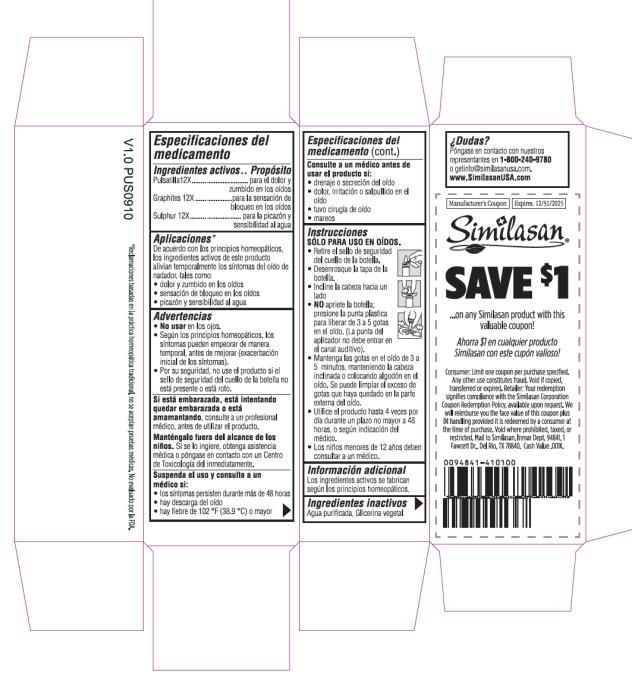 DRUG LABEL: Swimmers Ear Relief Ear Drops
NDC: 53799-278 | Form: LIQUID
Manufacturer: Similasan AG
Category: homeopathic | Type: HUMAN OTC DRUG LABEL
Date: 20201202

ACTIVE INGREDIENTS: ANEMONE PULSATILLA 12 [hp_X]/1 mL; GRAPHITE 12 [hp_X]/1 mL; SULFUR 12 [hp_X]/1 mL
INACTIVE INGREDIENTS: WATER; GLYCERIN

Swimmers Ear Relief

Drug Facts

Active ingredients

Pulsatilla 12X

Purpose

pain in ears, humming

Active ingredients

Graphites 12X

Purpose

blocked sensation in ears

Active ingredients

Sulphur 12X

Purpose

itchiness, sensitivity to water

Uses*

According to homeopathic principles, the active ingredients in this product temporarily relieve swimmer’s ear symptoms such as:

• pain in ears, humming

• blocked sensation in ears

• itchiness, sensitivity to water

Warnings

• Do not use in the eyes.

• According to homeopathic principles, symptoms may temporarily worsen before improving (Initial exacerbation of symptoms)

Keep out of reach of children.

If swallowed, get medical help or contact a Poison Control Center right away.

Stop use and ask a doctor if:

• symptoms persist for more than 48 hours

• there is discharge from the ear

• there is a fever of 102°F or greater

Ask a doctor before use if you have:

• ear drainage or discharge

• pain, irritation, or rash in the ear

• had ear surgery

• dizziness

Directions

FOR USE IN THE EAR ONLY.

• Remove tamper-evident seal from neck of bottle.

• Twist cap off bottle.

• Tilt head sideways.

• DON'T squeeze bottle, squeeze plastic tip to release 3 to 5 drops into ear (Tip of applicator should not enter ear canal).

• Keep drops in ear for 3 to 5 minutes by keeping head tilted or placing cotton in ear. Any excess drops can be wiped away from outer ear.

• Use up to 4 times daily for no more than 48 hours, or as directed by a doctor.

• Children under 12 years of age consult a doctor.

Other information

Active ingredients are manufactured according to homeopathic principles.

Inactive ingredient

Purified water, Vegetable glycerin

Questions?

Reach our representatives at 1-800-240-9780 or getinfo@similasanusa.com

www.SimilasanUSA.com

PRINCIPAL DISPLAY PANEL

Similasan
Swimmer’s Ear Relief
Ear Drops
10 ml/ 0.33 fl oz